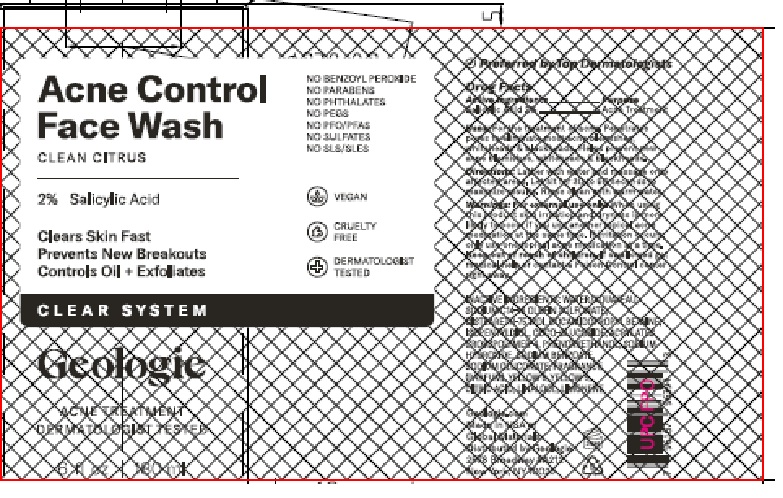 DRUG LABEL: Acne Control Face Wash
NDC: 54111-185 | Form: GEL
Manufacturer: Bentley Laboratories, LLC
Category: otc | Type: HUMAN OTC DRUG LABEL
Date: 20241128

ACTIVE INGREDIENTS: SALICYLIC ACID 2.0 g/100 mL
INACTIVE INGREDIENTS: WATER; SODIUM C14-16 OLEFIN SULFONATE; DISTEARETH-75 IPDI; COCAMIDOPROPYL BETAINE; ISOPENTYLDIOL; COCO-GLUCOSIDE; ACRYLATES CROSSPOLYMER-4; PHENOXYETHANOL; SODIUM HYDROXIDE; SODIUM BENZOATE; SODIUM GLUCONATE; YELLOW 6; YELLOW 5; CITRIC ACID; LINALOOL; LIMONENE, (+)-

Geologie Acne Control Face Wash

DRUG FACTS

Active Ingredients........... Salicylic Acid 2%

Purpose ............... Acne Treatment

INDICATIONS AND USAGE

Uses: For the treatment of acne. Penetrates pores to eliminate most acne blemishes, whiteheads & blackheads. Helps prevent new acne blemishes, whiteheads & blackheads.

DOSAGE AND ADMINISTRATION

Directions: Lather with water and massage onto affected areas. Let sit for 30 to 60 seconds to maximize results. Rinse clean with warm water.

WARNINGS

Warnings: For external use only. When using this product skin irritation and dryness is more likely to occur if you use another topical acne medication at the same time. If irritation occurs, only use one topical acne medication at a time.

KEEP OUT OF REACH OF CHILDREN

Keep out of the reach of children. If swallowed get medical help or contact a Poison Control center right away.

INACTIVE INGREDIENTS: WATER/AQUA/EAU,
SODIUM C14-16 OLEFIN SULFONATE,
DISTEARTH-75 IDPI, COCAMIDOPROPYL BETAINE,
ISOPENTYLDIOL, COCO-GLUCOSIDE, ACRYLATES
CROSSPOLYMER-4, PHENOXYETHANOL, SODIUM
HYDROXIDE, SODIUM BENZOATE,
SODIUM GLUCONATE, FRAGRANCE
(PARFUM), YELLOW 6, YELLOW 5,
CITRIC ACID, LINALOOL, LIMONENE

Geologie Acne Control Face Wash Labeling

Geologie

Acne Control Face Wash

CLEAN CITRUS

2% Salicylic Acid

6 fl oz 180 ml

Geologie.com
Made in USA of
Global Materials
Distributed by Geologie
2578 Broadway #A212
New York, NY 10025

res